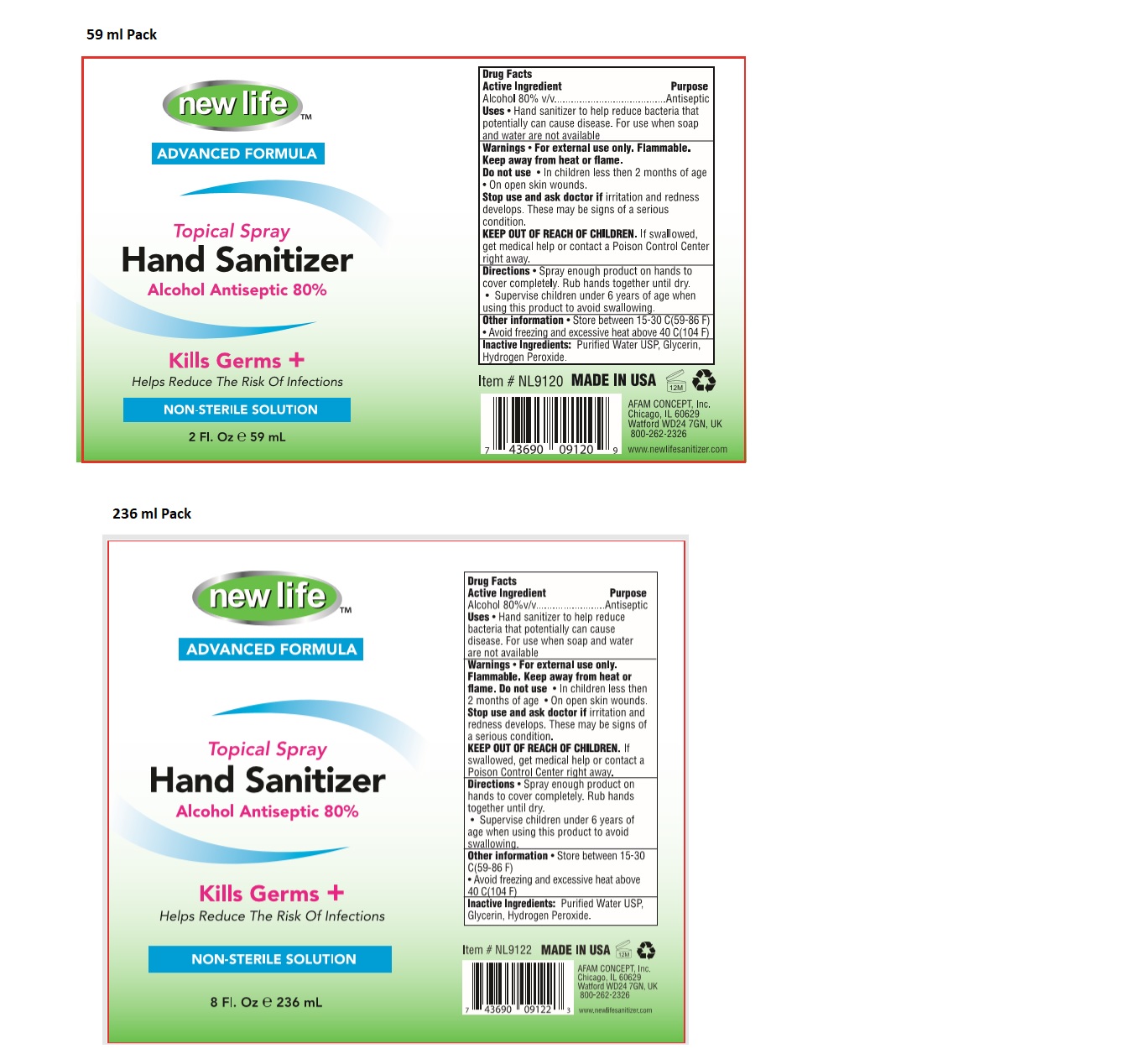 DRUG LABEL: New Life Advanced Formula Topical Hand sanitizer
NDC: 49681-200 | Form: SPRAY
Manufacturer: New Life Products, Inc.
Category: otc | Type: HUMAN OTC DRUG LABEL
Date: 20230202

ACTIVE INGREDIENTS: ALCOHOL 80 mL/100 mL
INACTIVE INGREDIENTS: WATER; GLYCERIN; HYDROGEN PEROXIDE

new life ™ ADVANCED FORMULA Topical Spray Hand Sanitizer

Active Ingredient

Alcohol 80% v/v

Purpose

Antiseptic

INDICATIONS AND USAGE

Uses • Hand sanitizer to help reduce bacteria that potentially can cause disease. For use when soap and water are not available

Warnings • For external use only. Flammable.

Keep away from heat or flame.

Do not use • In children less than 2 months of age

• On open skin wounds.

Stop use and ask doctor if irritation and redness develops. These may be signs of a serious condition.

KEEP OUT OF REACH OF CHILDREN. If swallowed, get medical help or contact a Poison Control Center right away.

DOSAGE AND ADMINISTRATION

Directions • Spray enough product on hands to cover completely. Rub hands together until dry.
• Supervise children under 6 years of age when using this product to avoid swallowing.

Other Information • Store between 15-30 C(59-86 F)
• Avoid freezing and excessive heat above 40 C(104 F)

Inactive ingredients: Purified Water USP, Glycerin, Hydrogen Peroxide.

Kills Germs +

Helps Reduce The Risk Of Infections

NON-STERILE SOLUTION

MADE IN USA

AFAM CONCEPT, Inc.

Chicago, IL 60629

Watford WD24 7GN, UK

800-262-2326

www.newlifesanitizer.com